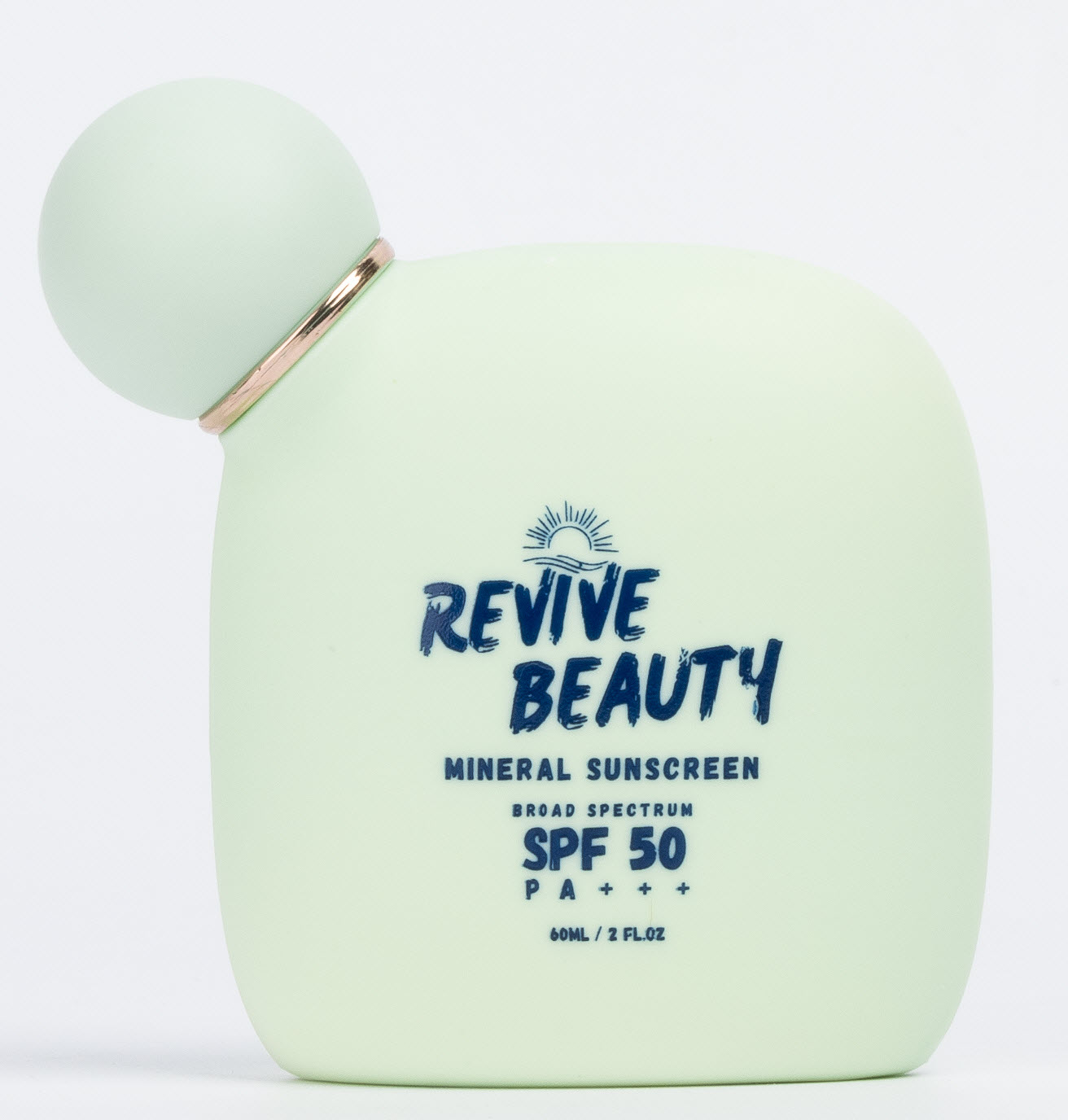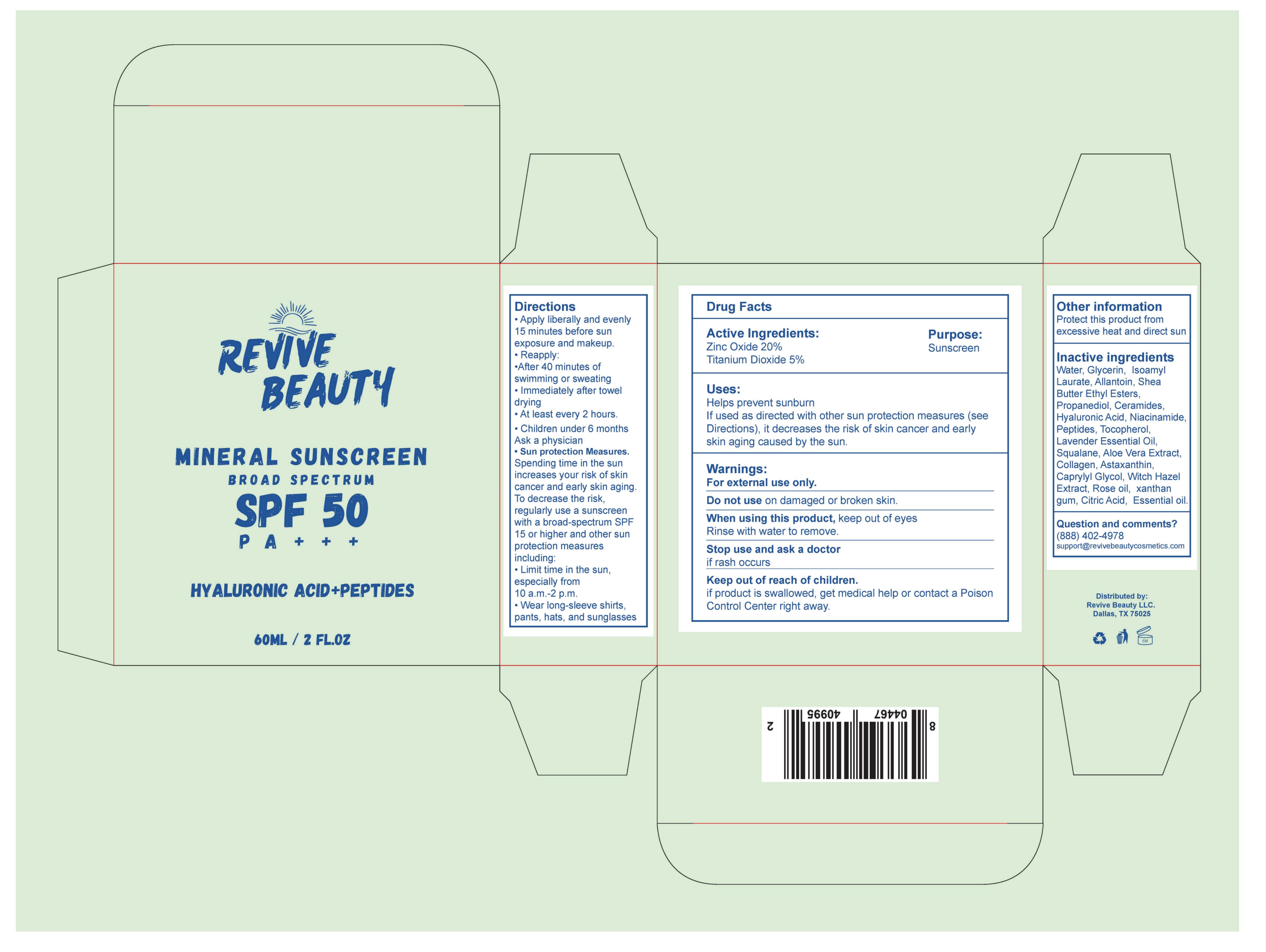 DRUG LABEL: Revive Beauty Mineral Sunscreen
NDC: 84798-001 | Form: CREAM
Manufacturer: Revive Beauty LLC
Category: otc | Type: HUMAN OTC DRUG LABEL
Date: 20241009

ACTIVE INGREDIENTS: ZINC OXIDE 20 g/100 mL
INACTIVE INGREDIENTS: ALOE VERA LEAF; ISOAMYL LAURATE; WATER; HYALURONIC ACID; LAVENDER OIL; SOY PROTEIN; ALLANTOIN; PROPANEDIOL; CUCUMBER SEED OIL; CITRIC ACID MONOHYDRATE; ASTAXANTHIN; NIACINAMIDE; XANTHAN GUM; GLYCERIN; TOCOPHEROL; CAPRYLYL GLYCOL; SHEA BUTTER ETHYL ESTERS; SQUALANE

Active Ingredients:

Zinc Oxide 20%

Titanium Dioxide 5%

Purpose

Sunscreen

INSTRUCTIONS FOR USE

Helps prevent sunburn

If used as directed with other sun protection measures (see Directions), it decreases the risk of skin cancer and early skin aging caused by the sun.

WARNINGS

For external use only.

Do not use on damaged or broken skin.

When using this product, keep out of eyes Rinse with water to remove.

Stop use and ask a doctor if rash occurs

Keep out of reach of children.

if product is swallowed, get medical help or contact a Poison Control Center right away.

INACTIVE INGREDIENT

Water, Glycerin, Zinc Oxide, Titanium Dioxide, Isoamyl Laurate, Hyaluronic Acid, Peptides, Allantoin, Shea Butter Ethyl Esters, Propanediol, Ceramide, Tocopherol, Lavender Essential Oil, Squalane, Aloe Vera Extract, Collagen, Astaxanthin, Hyaluronic acid, Niacinamide, Caprylyl Glycol, Witch Hazel Extract, Rose Extract, Olive Leaf Extract, Xanthan gum, Citric Acid, Soy Protein, Cucumber Essential oil.

Directions

• Apply liberally and evenly 15 minutes before sun exposure and makeup.
• Reapply:
•After 40 minutes of swimming or sweating
• Immediately after towel drying
• At least every 2 hours.
• Children under 6 months Ask a physician
• Sun protection Measures.
Spending time in the sun increases your risk of skin cancer and early skin aging.
To decrease the risk, regularly use a sunscreen with a broad-spectrum SPF 15 or higher and other sun protection measures
including:
• Limit time in the sun, especially from 10 a.m.-2 p.m.
• Wear long-sleeve shirts, pants, hats, and sunglasses

Keep out of reach of children.
if product is swallowed, get medical help or contact a Poison
Control Center right away.

Directions
• Apply liberally and evenly 15 minutes before sun exposure and makeup.
• Reapply:
•After 40 minutes of swimming or sweating
• Immediately after towel drying
• At least every 2 hours.
• Children under 6 months Ask a physician
• Sun protection Measures.
Spending time in the sun increases your risk of skin cancer and early skin aging.
To decrease the risk, regularly use a sunscreen with a broad-spectrum SPF 15 or higher and other sun protection measures
including:
• Limit time in the sun, especially from 10 a.m.-2 p.m.
• Wear long-sleeve shirts, pants, hats, and sunglasses